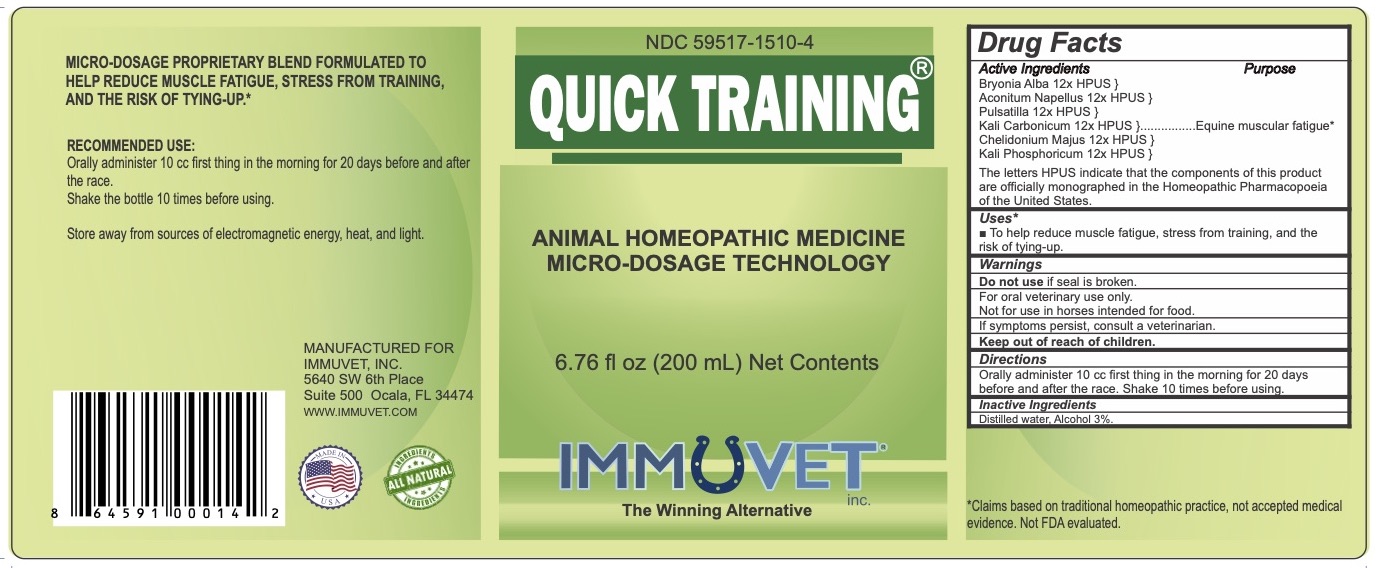 DRUG LABEL: Quick Training
NDC: 59517-1510 | Form: LIQUID
Manufacturer: Immuvet, Inc.
Category: homeopathic | Type: OTC ANIMAL DRUG LABEL
Date: 20251104

ACTIVE INGREDIENTS: BRYONIA ALBA ROOT 12 [hp_X]/1 mL; ACONITUM NAPELLUS 12 [hp_X]/1 mL; PULSATILLA ALPINA WHOLE 12 [hp_X]/1 mL; POTASSIUM CARBONATE 12 [hp_X]/1 mL; CHELIDONIUM MAJUS ROOT 12 [hp_X]/1 mL; POTASSIUM PHOSPHATE, DIBASIC 12 [hp_X]/1 mL
INACTIVE INGREDIENTS: ALCOHOL; WATER

Quick Training

PURPOSE

Micro-dosage proprietary blend formulated to help to reduce muscular fatigue, stress of training, and being tied up for horses in training.*

DIRECTIONS

Administer orally 10cc first thing in the morning for 20 days before and after the race. Shake 10 times before using.

ACTIVE INGREDIENTS

Bryonia Alba 12x HPUS
Aconitum Napellus 12x HPUS
Pulsatilla 12x HPUS
Kali Carbonicum 12x HPUS
Chelidonium Majus 12x HPUS
Kali Phosphoricum 12x HPUS

INACTIVE INGREDIENTS

Distilled water, Alcohol 5%

WARNINGS

Do not use if seal is broken.
For Oral Veterinary Use Only.
Not for use in Horses intended for food.
If problems persist, contact a veterinarian.
Keep out of reach of children.

OTHER INFORMATION

*Claims based on traditional homeopathic practice, not accepted medical evidence. Not FDA evaluated